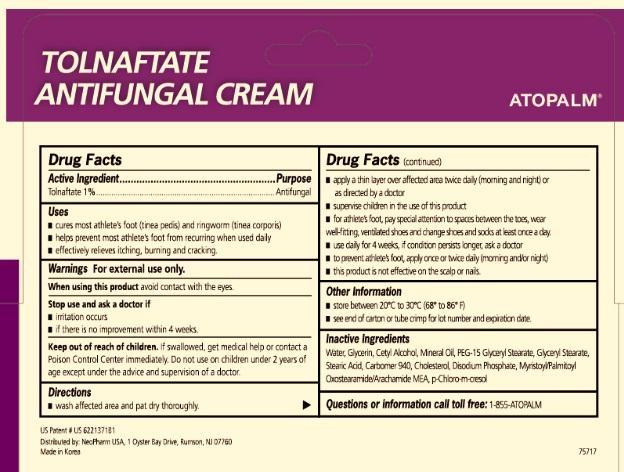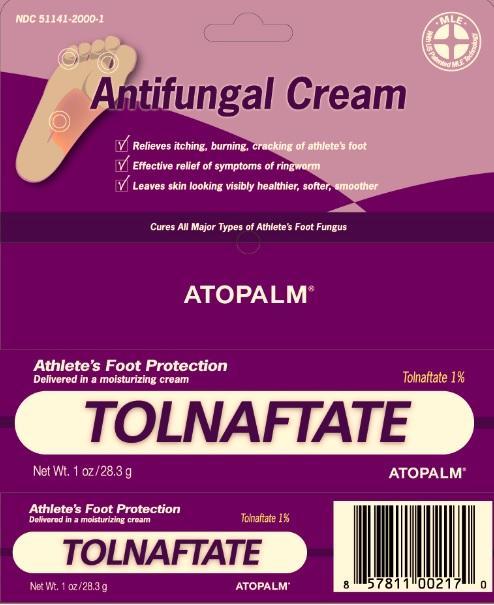 DRUG LABEL: ATOPALM TOLNAFTATE ANTIFUNGAL 
                        
NDC: 51141-2000 | Form: CREAM
Manufacturer: Neopharm Co., Ltd.
Category: otc | Type: HUMAN OTC DRUG LABEL
Date: 20150605

ACTIVE INGREDIENTS: TOLNAFTATE 1 g/100 g
INACTIVE INGREDIENTS: WATER; MINERAL OIL; GLYCERIN; PEG-15 GLYCERYL STEARATE; GLYCERYL MONOSTEARATE; STEARIC ACID; CARBOMER HOMOPOLYMER TYPE C; MYRISTOYL/PALMITOYL OXOSTEARAMIDE/ARACHAMIDE MEA; PHOSPHATE ION; CHLOROCRESOL

Atopalm Tolnaftate Antifungal Cream

Active Ingredients

Tolnaftate 1%

Purpose

Antifungal

Uses

cures most athlete's foot (tinea pedis) and ringworm (tinea corporis)

helps prevent most athletes foot from recurring when used daily

effectively relieves itching, burning and cracking.

Warnings

For external use only

When using this product

avoid contact with the eyes

Stop use and ask a doctor if

irritation occurs
if there is no improvement within 4 weeks

Keep out of reach of children.

If swallowed, get medical help or contact a Poison Control Center immediately. Do not use on children under 2 years of age except under the advice and supervision of a doctor.

Directions

wash affected area and pat dry thoroughly
apply a thin layer over affected area twice daily (morning and night) or as directed by a doctor
supervise children in the use of this product
for athlete's foot, pay special attention to spaces between the toes, wear well-fitting, ventilated shoes and change shoes and socks at least once a day.
use daily for 4 weeks, if condition persists longer, ask a doctor
to prevent athlete's foot, apply once or twice daily (morning and/or night)
this product not effective on the scalp or nails.

Other Information

store between 20 to 30 C (68 to 86)F

see end of carton or tube crimp for lot number and expiration date.

Inactive Ingredients

Water, glycerin, Cetyl alcohol, mineral oil, PEG-15 Glyeryl Stearate, Glyceryl Stearate, Stearic Acid, Carbomer 94-, Cholesterol, Disodium Phosphate, Myristoyl/Palmitoyl Oxostearamide/Archamide MEA, p-Chloro-m-cresol

Questions?

Call 1-855-ATOPALM

PACKAGE LABEL

Relieves itching, burning, cracking of athlete's foot
Effective relief of symptoms of ringworm
Tolnaftate 1%

ATOPALM
Antifungal Cream

with US Patented MLE Technology

Effective Infection Protection for cuts, scrapes and burns

ATOPALM
1% Tolnaftate Antifungal Cream

Cures All Major Types of Athletes Foot Fungus

Net wt. 1oz/28.3g

Distributed by: NeoPharm Co., Ltd 80 Wood Rd, 212 Camarillo, CA 93010

Made in Korea